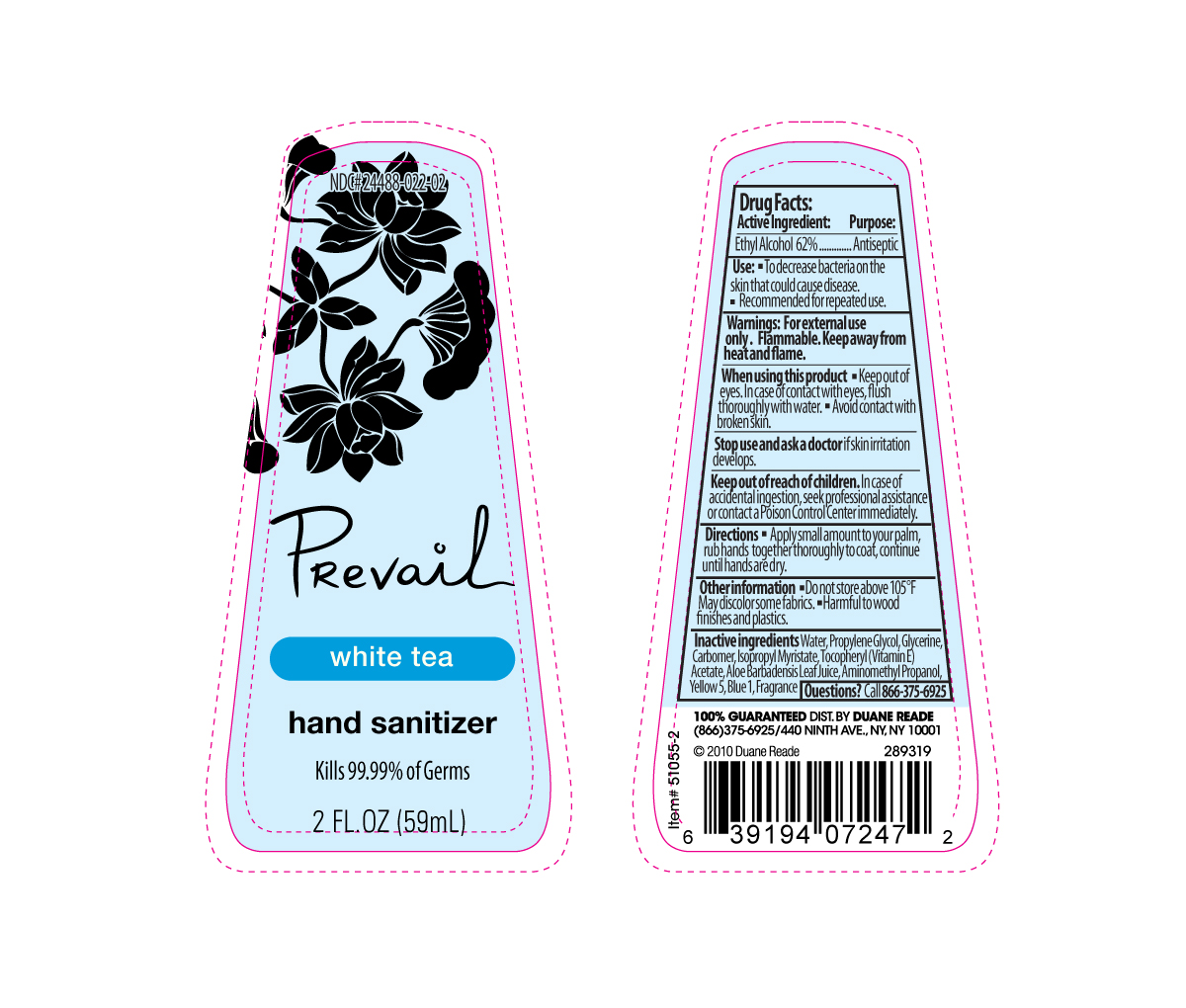 DRUG LABEL: Prevail
NDC: 24488-022 | Form: GEL
Manufacturer: Creation's Garden Natural Products, Inc
Category: otc | Type: HUMAN OTC DRUG LABEL
Date: 20110126

ACTIVE INGREDIENTS: ALCOHOL 36.58 mL/59 mL
INACTIVE INGREDIENTS: Water; PROPYLENE GLYCOL; GLYCERIN; CARBOMER HOMOPOLYMER TYPE C; ISOPROPYL MYRISTATE; ALPHA-TOCOPHEROL ACETATE; ALOE VERA LEAF; AMINOMETHYLPROPANOL; FD&C YELLOW NO. 5

Drug Facts

Active Ingredient

Ethyl Alcohol 62%.................................Antiseptic

Purpose

- To decrease bacteria on the skin that could cause disease.
- Recommended for repeated use.

Warnings

For external use only. Flammable. Keep away from heat and flame.

When using this product

- Keep out of eyes. In case of contact with eyes, flush throughly with water
- Avoid contact with broken skin.

STOP USE

If skin irritation develops.

Keep out of reach of children

In case of accidental ingestion, seek professional assistance or contact Poison Control Center immediately.

Directions

- Apply small amount to your palm, rub hands together throughly to coat, continue until hands are dry.

Other information

- Do not store above 105oF
- May discolor some fabrics
- Harmful to wood finishes and plastics

INACTIVE INGREDIENT

Water, Propylene Glycol, Glycerin, Carbomer, Isopropyl Myristate, Tocopheryl (Vitamin E) Acetate, Aloe Barbadensis Leaf Juice, Aminomethyl Propanol, Yellow 5, Fragrance

Questions

Call (866) 375-6925

PACKAGE LABEL

place holder text